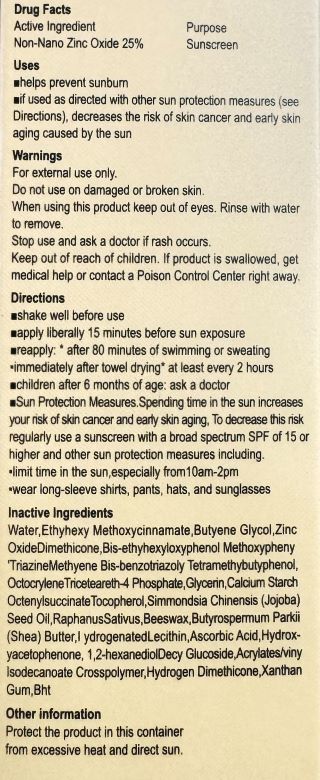 DRUG LABEL: Face and Body Sunscreen
NDC: 87092-001 | Form: CREAM
Manufacturer: Guangzhou Shengyanghui Industrial Trading Co., Ltd
Category: otc | Type: HUMAN OTC DRUG LABEL
Date: 20251208

ACTIVE INGREDIENTS: ZINC OXIDE 25 g/100 g
INACTIVE INGREDIENTS: GLYCERIN; ACRYLATES/VINYL ISODECANOATE CROSSPOLYMER (10000 MPA.S NEUTRALIZED AT 0.5%); 1,2-HEXANEDIOL; DECYL GLUCOSIDE; HYDROGEN DIMETHICONE (20 CST); HYDROXYACETOPHENONE; SIMMONDSIA CHINENSIS (JOJOBA) SEED OIL; ALUMINUM STARCH OCTENYLSUCCINATE; ETHYLHEXYL METHOXYCINNAMATE; ASCORBIC ACID; DIMETHICONE; GLUTATHIONE; METHYLENE BIS-BENZOTRIAZOLYL TETRAMETHYLBUTYLPHENOL; XANTHAN GUM; WATER; RAPHANUS SATIVUS; BUTYLENE GLYCOL; BEESWAX; CALCIUM; BIS-ETHYLHEXYLOXYPHENOL METHOXYPHENYL TRIAZINE; BHT; BUTYROSPERMUM PARKII (SHEA) BUTTER; TOCOPHEROL; HYDROGENATED SOYBEAN LECITHIN

ACTIVE INGREDIENT

Non-Nano Zinc Oxide 25%

PURPOSE

helps prevent sunburn.if used as directed with other sun protection measures (seeDirections), decreases the risk of skin cancer and early skinaging caused by the sun

Keep out of reach of children. lf product is swallowed, getmedical help or contact a Poison Control Center right away.

INSTRUCTIONS FOR USE

shake well before use，apply liberally 15 minutes before sun exposure，reapply:* after 80 minutes of swimming or sweating*immediately after towel drying* at least every 2 hours，children after 6 months of age: ask a doctor，Sun Protection Measures,Spendina time in the sun increases
your risk of skin cancer and eary skin aging, To decrease this riskregularly use a sunscreen with a broad spectrum SPF of 15 ohigher and other sun protection measures including.
limit time in the sun,especially from10am-2pm
wear long-sleeve shirts, pants, hats, and sunglasses

WARNINGS AND PRECAUTIONS

For external use only.Do not use on damaged or broken skin.When using this product keep out of eyes. Rinse with waterto remove.
Stop use and ask a doctor if rash occurs.Keep out of reach of children. lf product is swallowed, getmedical help or contact a Poison Control Center right away.

INACTIVE INGREDIENT

Water,Ethyhexy Methoxycinnamate,Butyene Glycol,ZincOxideDimethicone,Bis-ethyhexyloxyphenol Methoxypheny'TriazineMethyene Bis-benzotriazoly Tetramethybutyphenol,OctocryleneTriceteareth-4 Phosphate,Glycerin,Calcium StarchOctenylsuccinateTocopherol,Simmondsia Chinensis (Jojoba)Seed Oil,RaphanusSativus,Beeswax,Butyrospermum Parkii(Shea) Butter,l ydrogenatedLecithin,Ascorbic Acid,Hydroxyacetophenone, 1,2-hexanediolDecy Glucoside,Acrylates/vinyIsodecanoate Crosspolymer,Hydrogen Dimethicone,XanthanGum,Bht

INDICATIONS AND USAGE

helps prevent sunburn.

if used as directed with other sun protection measures (seeDirections), decreases the risk of skin cancer and early skinaging caused by the sun

WARNINGS

For external use only.Do not use on damaged or broken skin.When using this product keep out of eyes. Rinse with waterto remove.Stop use and ask a doctor if rash occurs.Keep out of reach of children. lf product is swallowed, getmedical help or contact a Poison Control Center right away.

DOSAGE AND ADMINISTRATION

apply liberally 15 minutes before sun exposure

reapply: * after 80 minutes of swimming or sweatingimmediately after towel drying* at least every 2 hours